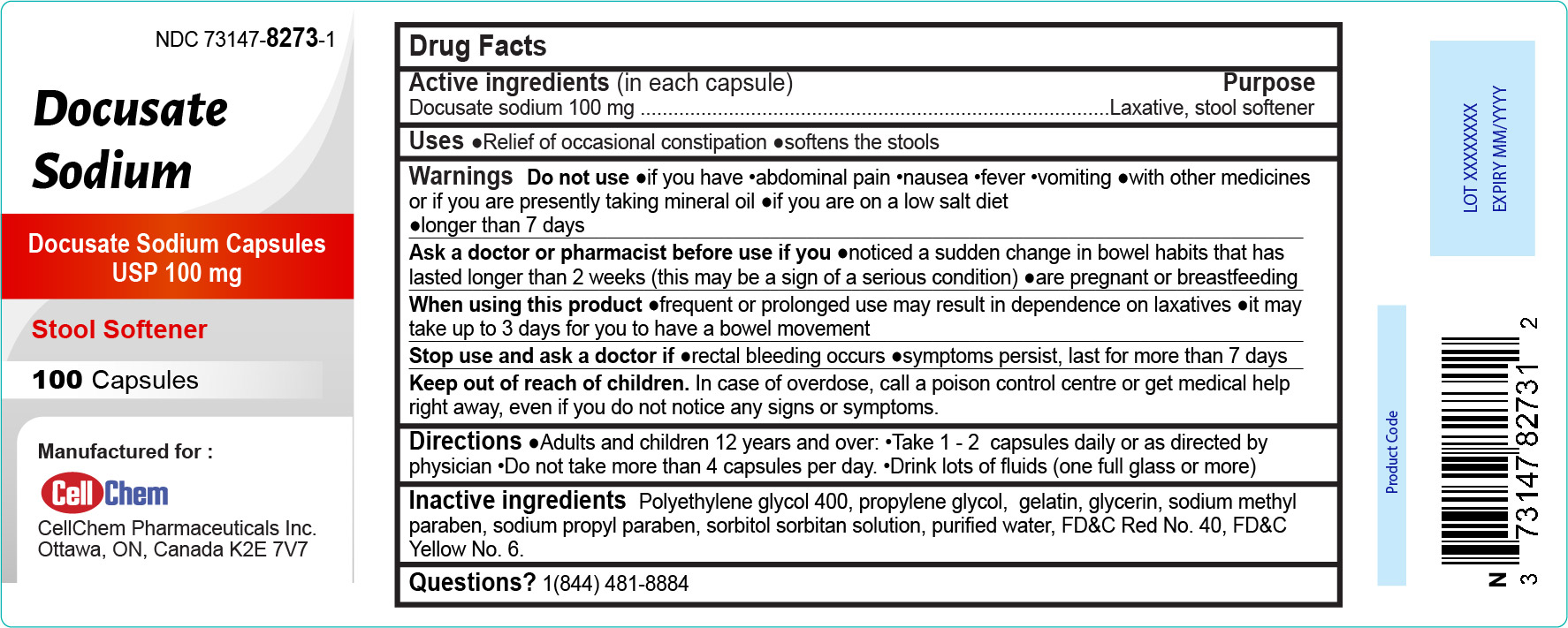 DRUG LABEL: DOCUSATE SODIUM
NDC: 73147-8273 | Form: CAPSULE
Manufacturer: Cellchem Pharmaceutical Inc
Category: otc | Type: HUMAN OTC DRUG LABEL
Date: 20231221

ACTIVE INGREDIENTS: DOCUSATE SODIUM 100 mg/1 1
INACTIVE INGREDIENTS: PROPYLENE GLYCOL; GELATIN; GLYCERIN; METHYLPARABEN SODIUM; PROPYLPARABEN SODIUM; SORBITOL SOLUTION; FD&C RED NO. 40; FD&C YELLOW NO. 6; POLYETHYLENE GLYCOL 400; WATER

Active Ingredient (in each capsule) Purpose

Docusate sodium 100 mg................................................Laxative, stool softener

PURPOSE

Stool Softener

Uses

- Relief of occasional constipation
- softens the stools

Warnings

Do not use

- if you have
  - abdominal pain
  - nausea
  - fever
  - vomiting
- with other medicines or if you are presently taking mineral oil
- if you are on a low salt diet
- longer than 7 days

When using this product

- frequent or prolonged use may result in dependence on laxatives
- it may take up to 3 days for you to have a bowel movement

Stop use and ask a doctor if

- rectal bleeding occurs
- symptoms persist, last for more than 7 days

Keep out of reach of children. In case of overdose, call a poison control centre or get medical help right away, even if you do not notice any signs or symptoms.

Directions

- Adults and children 12 years and over:
- Take 1 - 2 capsules daily or as directed by physician
- Do not take more than 4 capsules per day.
- Drink lots of fluids (one full glass or more)

Other information

- Questions ?

1(844) 481-8884

Inactive ingredients

Polyethylene glycol 400, propylene glycol, gelatin, glycerin, sodium methyl paraben, sodium propyl paraben, sorbitol sorbitan solution, purified water, FD&C Red No. 40, FD&C Yellow No. 6.

Manufactured for :
CellChem Pharmaceuticals Inc.
Ottawa, ON, Canada K2E 7V7